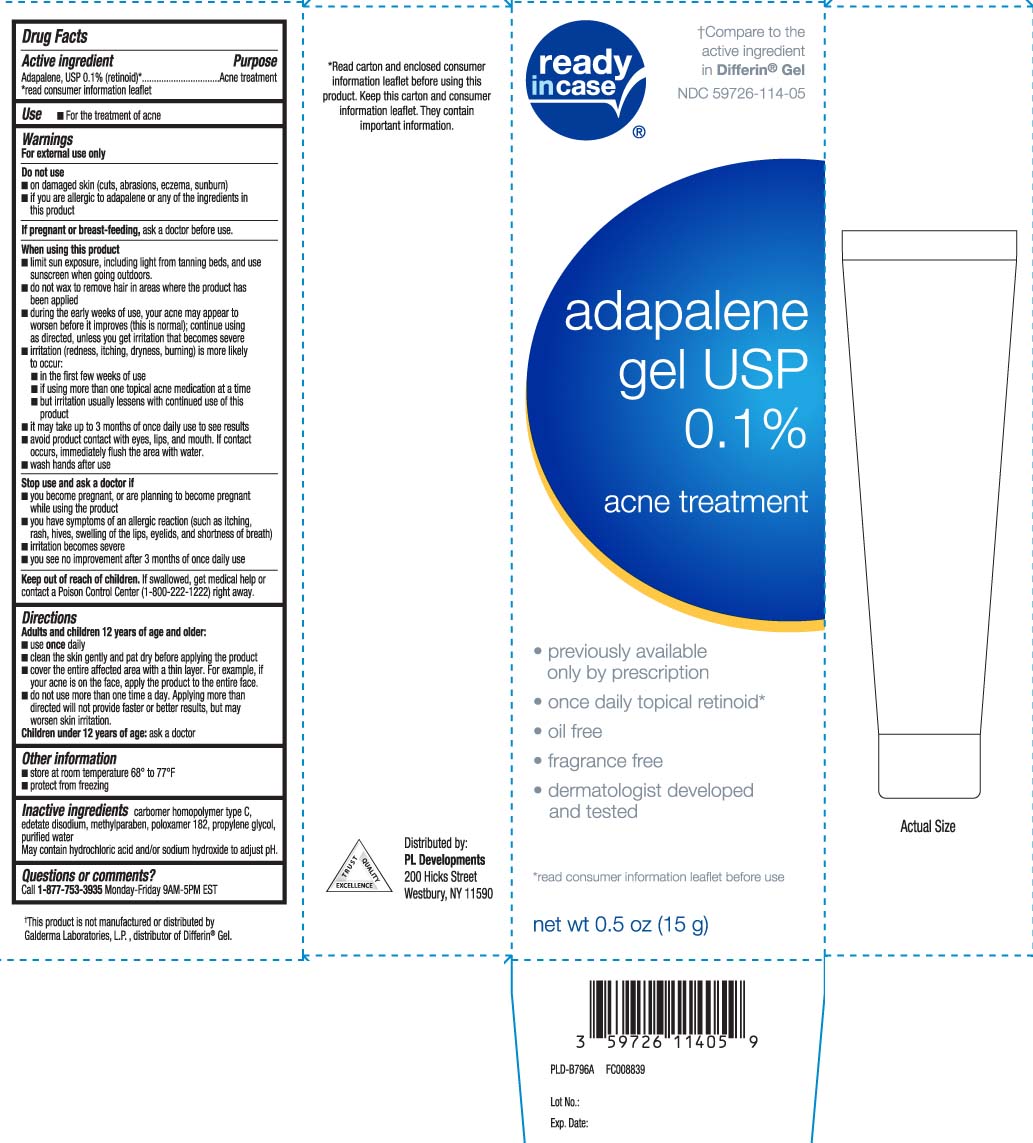 DRUG LABEL: Adapalene
NDC: 59726-114 | Form: GEL
Manufacturer: P & L Development, LLC
Category: otc | Type: HUMAN OTC DRUG LABEL
Date: 20251216

ACTIVE INGREDIENTS: ADAPALENE 1 mg/1 g
INACTIVE INGREDIENTS: CARBOMER HOMOPOLYMER TYPE C (ALLYL PENTAERYTHRITOL CROSSLINKED); EDETATE DISODIUM; METHYLPARABEN; POLOXAMER 182; PROPYLENE GLYCOL; WATER; SODIUM HYDROXIDE

Adapalene Gel USP 0 1 percent ENE 0 5 OZ DELISTED

Active ingredient

Adapalene USP 0.1% (retinoid)*

*read consumer information leaflet

Purpose

Acne treatment

Use

- For the treatment of acne

Warnings

For external use only

Do not use

- on damaged skin (cuts, abrasions eczema, sunburn)
- if you are allergic to adapalene or any of the ingredients in this product

Pregnancy/Breastfeeding,

ask a doctor before use.

When using this product

- limit sun exposure, including light from tanning beds, and use sunscreen when going outdoors.
- do not wax to remove hair in areas where the product has been applied
- during the early weeks of use, your acne may appear to worsen before it improves (this is normal); continue using as directed, unless you get irritation that become severe
- irritation (redness, itching, dryness, burning) is more likely to occur:
  - in the first few weeks of use
  - if using more than one topical acne medication at a time
  - but irritation usually lessens with continued use of this product
- it may take up to 3 months of once daily use to see result
- avoid product contact eyes, lips, and month. If contact occurs immediately flush the area with water.
- wash hands after use

Stop use and ask a doctor if

- you become pregnant, or planning to become pregnant while using this product
- you have symptoms of an allergic reaction (such as itching, rash, hives, swelling of the lips, eyelids, and shortness of breath)
- irritation become severe
- you see no improvement after 3 months of once daily use

Keep out of reach of children.

If swallowed, get medical help or contact a Poison Control Center (1-800-222-1222) right away.

Directions

Adults and children 12 years of age and older:

- use once daily
- clean the skin gently and pat dry before applying the product
- cover the entire affected area with a thin layer. For example, if your acne in on the face, apply the product to the entire face.
- do not use more than one time a day. Applying more than directed will not provide faster or better results, but may worsen skin irritation.
- Children under 12 years of age: ask a doctor

Other information

- store at rooms temperature 68º to 77ºF
- protect from freezing

Inactive ingredients

carbomer homopolymertype C, edetate disodium, methylparabem, poloxamer 182, propylene glycol, purified water. May contain hydrochloric acid and/or sodium hydroxide to adjust pH.

Questions or comments?

Call 1-877-753-3935 Monday-Friday 9AM-5PM EST

Principal Display Panel

†Compare to the active ingredient in Differin® Gel

adapalene Gel USP, 0.1%

acne Treatment

- Previously available only by prescription
- Once daily topical retinoid*
- Oil free
- fragrance free
- Dermatologist developed and tested

net wt oz (g)

*Read consumer information leaflet before use

†This product is not manufactured or distributed by Galderma Laboratories, L.P. distributor of Differin® Gel.

Distributed by:

PL Developments

200 Hicks Street

Westbury, NY 11590

Product Label

READYinCASE Acne Treatment